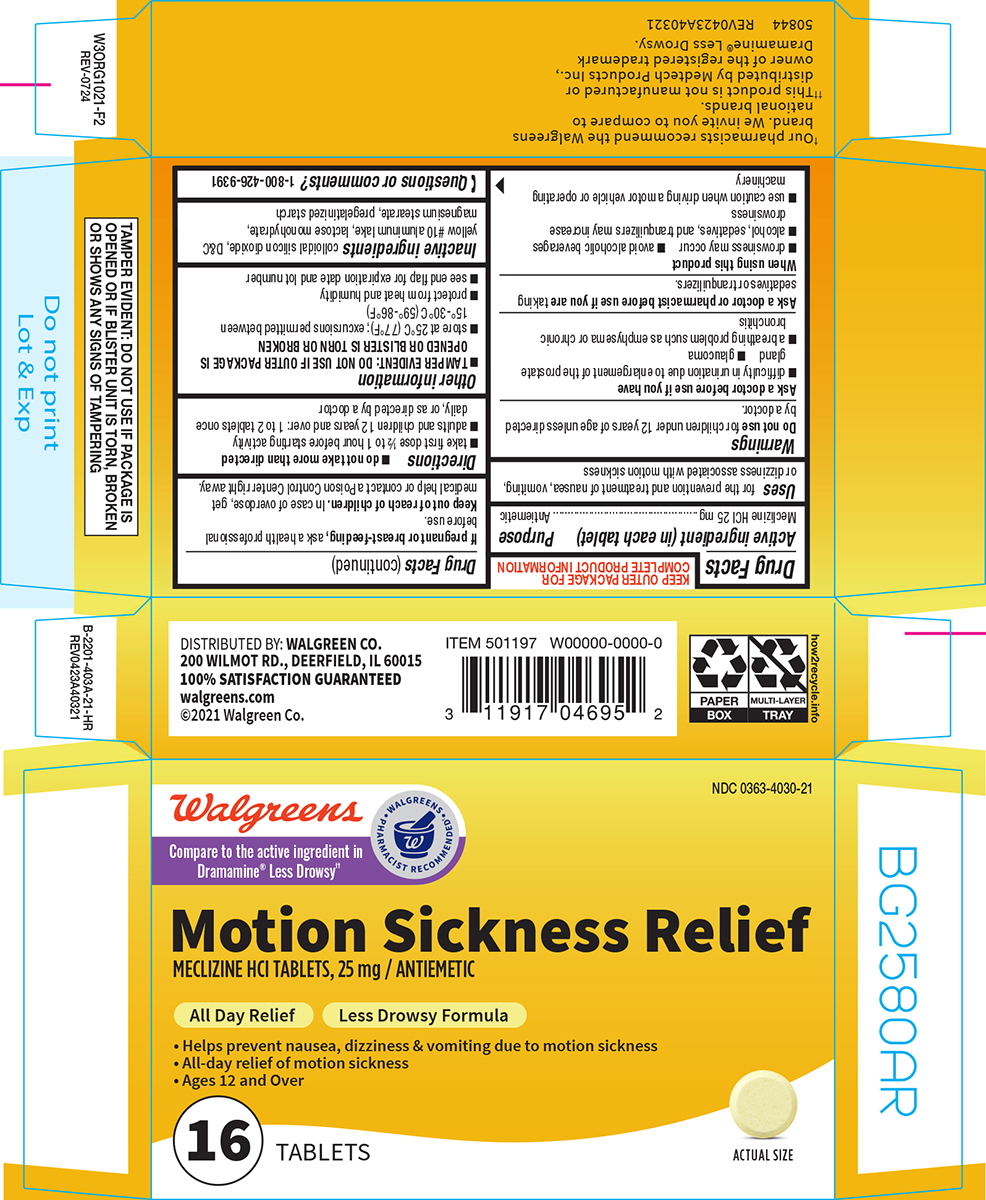 DRUG LABEL: Motion Sickness Relief
NDC: 0363-4030 | Form: TABLET
Manufacturer: Walgreen Company
Category: otc | Type: HUMAN OTC DRUG LABEL
Date: 20251105

ACTIVE INGREDIENTS: MECLIZINE HYDROCHLORIDE 25 mg/1 1
INACTIVE INGREDIENTS: SILICON DIOXIDE; D&C YELLOW NO. 10 ALUMINUM LAKE; LACTOSE MONOHYDRATE; MAGNESIUM STEARATE; STARCH, CORN

Walgreens 44-403A

Active ingredient (in each tablet)

Meclizine HCl 25 mg

Purpose

Antiemetic

Uses

for the prevention and treatment of nausea, vomiting, or dizziness associated with motion sickness

Warnings

Do not use

for children under 12 years of age unless directed by a doctor.

Ask a doctor before use if you have

- glaucoma
- difficulty in urination due to enlargement of the prostate gland
- a breathing problem such as emphysema or chronic bronchitis

Ask a doctor or pharmacist before use if you are

taking sedatives or tranquilizers.

When using this product

- alcohol, sedatives, and tranquilizers may increase drowsiness
- drowsiness may occur
- use caution when driving a motor vehicle or operating machinery
- avoid alcoholic beverages

If pregnant or breast-feeding,

ask a health professional before use.

Keep out of reach of children.

In case of overdose, get medical help or contact a Poison Control Center right away.

Directions

- do not take more than directed
- take first dose 1/2 to 1 hour before starting activity
- adults and children 12 years and over: 1 to 2 tablets once daily, or as directed by a doctor

Other information

- TAMPER EVIDENT: DO NOT USE IF OUTER PACKAGE IS OPENED OR BLISTER IS TORN OR BROKEN
- store at 25°C (77°F); excursions permitted between 15°-30°C (59°-86°F)
- protect from heat and humidity
- see end flap for expiration date and lot number

Inactive ingredients

colloidal silicon dioxide, D&C yellow #10 aluminum lake, lactose monohydrate, magnesium stearate, pregelatinized starch

Questions or comments?

1-800-426-9391

Principal display panel

Walgreens

• WALGREENS •
PHARMACIST RECOMMENDED†

Compare to the active ingredient in
Dramamine® Less Drowsy††

NDC 0363-4030-21

Motion Sickness Relief
MECLIZINE HCl TABLETS, 25 mg / ANTIEMETIC

All Day Relief Less Drowsy Formula

• Helps prevent nausea, dizziness & vomiting due to motion sickness
• All-day relief of motion sickness
• Ages 12 and Over

16 TABLETS

ACTUAL SIZE

†Our pharmacists recommend the Walgreens
brand. We invite you to compare to
national brands.
††This product is not manufactured or
distributed by Medtech Products Inc.,
owner of the registered trademark
Dramamine® Less Drowsy.

50844 REV0423A40321

TAMPER EVIDENT: DO NOT USE IF PACKAGE IS
OPENED OR IF BLISTER UNIT IS TORN, BROKEN
OR SHOWS ANY SIGNS OF TAMPERING

DISTRIBUTED BY: WALGREEN CO.
200 WILMOT RD., DEERFIELD, IL 60015
100% SATISFACTION GUARANTEED
walgreens.com
©2021 Walgreen Co.

Walgreens 44-403A